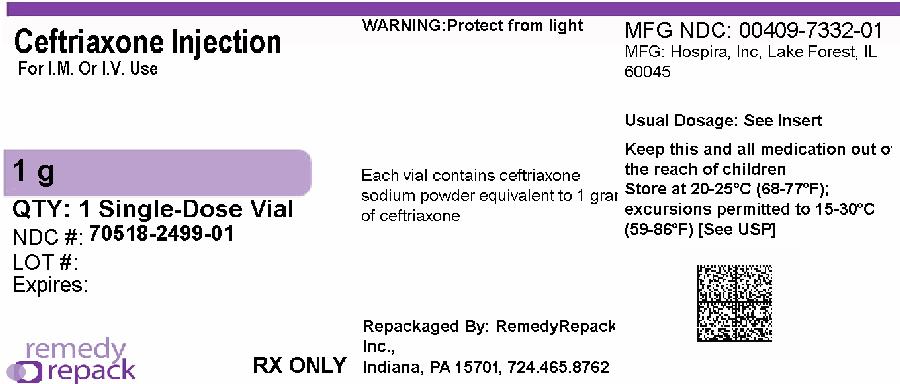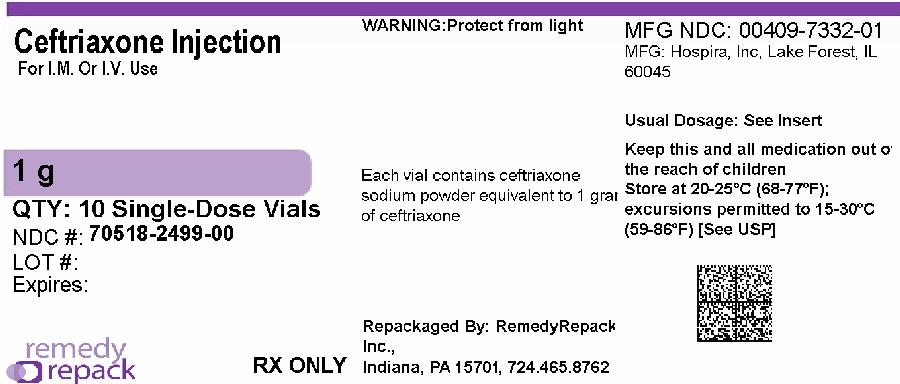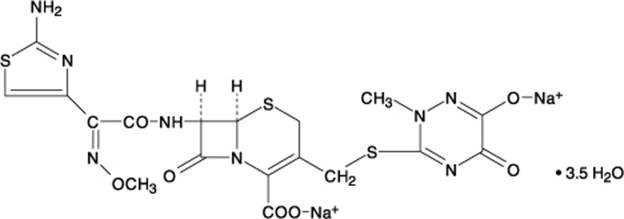 DRUG LABEL: Ceftriaxone Sodium
NDC: 70518-2499 | Form: INJECTION, POWDER, FOR SOLUTION
Manufacturer: REMEDYREPACK INC.
Category: prescription | Type: HUMAN PRESCRIPTION DRUG LABEL
Date: 20260206

ACTIVE INGREDIENTS: CEFTRIAXONE SODIUM 1 g/1 1

Ceftriaxone for Injection, USP

Rx Only

To reduce the development of drug-resistant bacteria and maintain the effectiveness of ceftriaxone for injection, and other antibacterial drugs, ceftriaxone for injection should be used only to treat or prevent infections that are proven or strongly suspected to be caused by bacteria.

DESCRIPTION

Ceftriaxone for injection, USP is a sterile, semisynthetic, broad-spectrum cephalosporin antibiotic for intravenous or intramuscular administration. Ceftriaxone sodium is (6 R, 7 R)-7-[2-(2-Amino-4-thiazolyl) glyoxylamido]-8-oxo-3-[[(1,2,5,6-tetrahydro-2-methyl-5,6-dioxo- as-triazin-3-yl)thio]methyl]-5-thia-1-azabicyclo[4.2.0]oct-2-ene-2-carboxylic acid, 7^2-(Z)-(O-methyloxime), disodium salt, sesquaterhydrate.

The chemical formula of ceftriaxone sodium is C18H16N8Na2O7S3•3.5H2O. It has a calculated molecular weight of 661.60 and the following structural formula:

Ceftriaxone sodium is a white to yellowish crystalline powder which is readily soluble in water, sparingly soluble in methanol and very slightly soluble in ethanol. The pH of a 1% aqueous solution is approximately 6.7. The color of ceftriaxone sodium solutions ranges from light yellow to amber, depending on the length of storage, concentration and diluent used.

Each vial contains ceftriaxone sodium equivalent to 250 mg, 500 mg, 1 gram or 2 grams of ceftriaxone activity. Ceftriaxone sodium contains approximately 83 mg (3.6 mEq) of sodium per gram of ceftriaxone activity.

CLINICAL PHARMACOLOGY

Average plasma concentrations of ceftriaxone following a single 30-minute intravenous (IV) infusion of a 0.5, 1 or 2 g dose and intramuscular (IM) administration of a single 0.5 (250 mg/mL or 350 mg/mL concentrations) or 1 g dose in healthy subjects are presented in Table 1.

Table 1. Ceftriaxone Plasma Concentrations after Single Dose Administration
 | Average Plasma Concentrations (mcg/mL)
Dose/Route | 0.5 hour | 1 hour | 2 hour | 4 hour | 6 hour | 8 hour | 12 hour | 16 hour | 24 hour
0.5 g IV | 82 | 59 | 48 | 37 | 29 | 23 | 15 | 10 | 5
0.5 g IM; 250 mg/mL | 22 | 33 | 38 | 35 | 30 | 26 | 16 | ND | 5
0.5 g IM; 350 mg/mL | 20 | 32 | 38 | 34 | 31 | 24 | 16 | ND | 5
1 g IV | 151 | 111 | 88 | 67 | 53 | 43 | 28 | 18 | 9
1 g IM | 40 | 68 | 76 | 68 | 56 | 44 | 29 | ND | ND
2 g lV | 257 | 192 | 154 | 117 | 89 | 74 | 46 | 31 | 15
ND = Not determined.

* IV doses were infused at a constant rate over 30 minutes.

Ceftriaxone was completely absorbed following IM administration with mean maximum plasma concentrations occurring between 2 and 3 hours post-dose. Multiple IV or IM doses ranging from 0.5 to 2 g at 12 to 24 hour intervals resulted in 15% to 36% accumulation of ceftriaxone above single dose values.

Ceftriaxone concentrations in urine are shown in Table 2.

Table 2. Urinary Concentrations of Ceftriaxone after Single Dose Administration
Dose/Route | Average Urinary Concentrations (mcg/mL)
Dose/Route | 0 to 2 hour | 2 to 4 hour | 4 to 8 hour | 8 to 12 hour | 12 to 24 hour | 24 to 48 hour
0.5 g IV | 526 | 366 | 142 | 87 | 70 | 15
0.5 g IM | 115 | 425 | 308 | 127 | 96 | 28
1 g IV | 995 | 855 | 293 | 147 | 132 | 32
1 g IM | 504 | 628 | 418 | 237 | ND | ND
2 g IV | 2692 | 1976 | 757 | 274 | 198 | 40
ND = Not determined.

Thirty-three percent to 67% of a ceftriaxone dose was excreted in the urine as unchanged drug and the remainder was secreted in the bile and ultimately found in the feces as microbiologically inactive compounds. After a 1 g IV dose, average concentrations of ceftriaxone, determined from 1 to 3 hours after dosing, were 581 mcg/mL in the gallbladder bile, 788 mcg/mL in the common duct bile, 898 mcg/mL in the cystic duct bile, 78.2 mcg/g in the gallbladder wall and 62.1 mcg/mL in the concurrent plasma.

Over a 0.15 to 3 g dose range in healthy adult subjects, the values of elimination half-life ranged from 5.8 to 8.7 hours; apparent volume of distribution from 5.78 to 13.5 L; plasma clearance from 0.58 to 1.45 L/hour; and renal clearance from 0.32 to 0.73 L/hour. Ceftriaxone is reversibly bound to human plasma proteins, and the binding decreased from a value of 95% bound at plasma concentrations of < 25 mcg/mL to a value of 85% bound at 300 mcg/mL. Ceftriaxone crosses the blood placenta barrier.

The average values of maximum plasma concentration, elimination half-life, plasma clearance and volume of distribution after a 50 mg/kg IV dose and after a 75 mg/kg IV dose in pediatric patients suffering from bacterial meningitis are shown in Table 3. Ceftriaxone penetrated the inflamed meninges of infants and pediatric patients; CSF concentrations after a 50 mg/kg IV dose and after a 75 mg/kg IV dose are also shown in Table 3.

Table 3. Average Pharmacokinetic Parameters of Ceftriaxone in Pediatric Patients with Meningitis
 | 50 mg/kg IV | 75 mg/kg IV
Maximum Plasma; Concentrations (mcg/mL) | 216 | 275
Elimination Half-life (hour) | 4.6 | 4.3
Plasma Clearance (mL/hour/kg) | 49 | 60
Volume of Distribution (mL/kg) | 338 | 373
CSF Concentration –; inflamed meninges (mcg/mL) | 5.6 | 6.4
Range (mcg/mL) | 1.3 to 18.5 | 1.3 to 44
Time after dose (hour) | 3.7 (± 1.6) | 3.3 (± 1.4)

Compared to that in healthy adult subjects, the pharmacokinetics of ceftriaxone were only minimally altered in elderly subjects and in patients with renal impairment or hepatic dysfunction (Table 4); therefore, dosage adjustments are not necessary for these patients with ceftriaxone dosages up to 2 g per day. Ceftriaxone was not removed to any significant extent from the plasma by hemodialysis; in six of 26 dialysis patients, the elimination rate of ceftriaxone was markedly reduced.

Table 4. Average Pharmacokinetic Parameters of Ceftriaxone in Humans
Subject Group | Elimination; Half-Life; (hour) | Plasma; Clearance; (L/hour) | Volume of; Distribution; (L)
Healthy Subjects | 5.8 to 8.7 | 0.58 to 1.45 | 5.8 to 13.5
Elderly Subjects; (mean age, 70.5 year) | 8.9 | 0.83 | 10.7
Patients With; Renal Impairment
Hemodialysis Patients; (0 to 5 mL/min) | 14.7 | 0.65 | 13.7
Severe (5 to 15 mL/min) | 15.7 | 0.56 | 12.5
Moderate (16 to 30 mL/min) | 11.4 | 0.72 | 11.8
Mild (31 to 60 mL/min) | 12.4 | 0.70 | 13.3
Patients With; Liver Disease | 8.8 | 1.1 | 13.6

* Creatinine clearance.

The elimination of ceftriaxone is not altered when ceftriaxone is co-administered with probenecid.

Pharmacokinetics in the Middle Ear Fluid

In one study, total ceftriaxone concentrations (bound and unbound) were measured in middle ear fluid obtained during the insertion of tympanostomy tubes in 42 pediatric patients with otitis media. Sampling times were from 1 to 50 hours after a single intramuscular injection of 50 mg/kg of ceftriaxone. Mean (±SD) ceftriaxone levels in the middle ear reached a peak of 35 (±12) mcg/mL at 24 hours, and remained at 19 (±7) mcg/mL at 48 hours. Based on middle ear fluid ceftriaxone concentrations in the 23 to 25 hour and the 46 to 50 hour sampling time intervals, a half-life of 25 hours was calculated. Ceftriaxone is highly bound to plasma proteins. The extent of binding to proteins in the middle ear fluid is unknown.

Interaction with Calcium

Two in vitrostudies, one using adult plasma and the other neonatal plasma from umbilical cord blood have been carried out to assess interaction of ceftriaxone and calcium. Ceftriaxone concentrations up to 1 mM (in excess of concentrations achieved in vivofollowing administration of 2 grams ceftriaxone infused over 30 minutes) were used in combination with calcium concentrations up to 12 mM (48 mg/dL). Recovery of ceftriaxone from plasma was reduced with calcium concentrations of 6 mM (24 mg/dL) or higher in adult plasma or 4 mM (16 mg/dL) or higher in neonatal plasma. This may be reflective of ceftriaxone-calcium precipitation.

Microbiology

Mechanism of Action

Ceftriaxone is a bactericidal agent that acts by inhibition of bacterial cell wall synthesis. Ceftriaxone has activity in the presence of some beta-lactamases, both penicillinases and cephalosporinases, of Gram-negative and Grampositive bacteria.

Mechanism of Resistance

Resistance to ceftriaxone is primarily through hydrolysis by beta-lactamase, alteration of penicillin-binding proteins (PBPs), and decreased permeability.

Interaction with Other Antimicrobials

In an in vitro study antagonistic effects have been observed with the combination of chloramphenicol and ceftriaxone.

Antibacterial Activity

Ceftriaxone has been shown to be active against most isolates of the following bacteria, both in vitro and in clinical infections as described in the INDICATIONS AND USAGE (1)section:

- Gram-negative Bacteria

Acinetobacter calcoaceticus

Enterobacter aerogenes

Enterobacter cloacae

Escherichia coli

Haemophilus influenzae

Haemophilus parainfluenzae

Klebsiella oxytoca

Klebsiella pneumoniae

Moraxella catarrhalis

Morganella morganii

Neisseria gonorrhoeae

Neisseria meningitidis

Proteus mirabilis

Proteus vulgaris

Pseudomonas aeruginosa

Serratia marcescens

- Gram-positive Bacteria

Staphylococcus aureus

Staphylococcus epidermidis

Streptococcus pneumoniae

Streptococcus pyogenes

Viridans group streptococci

- Anaerobic Bacteria

Bacteroides fragilis

Clostridiumspecies

Peptostreptococcusspecies

The following in vitrodata are available, but their clinical significance is unknown. At least 90 percent of the following microorganisms exhibit an in vitrominimum inhibitory concentration (MIC) less than or equal to the susceptible breakpoint for ceftriaxone. However, the efficacy of ceftriaxone in treating clinical infections due to these microorganisms has not beenestablished in adequate and well-controlled clinical trials.

- Gram-negative Bacteria

Citrobacter diversus

Citrobacter freundii

Providenciaspecies (including Providencia rettgeri)

Salmonellaspecies (including Salmonella typhi)

Shigellaspecies

- Gram-positive Bacteria

Streptococcus agalactiae

- Anaerobic Bacteria

Porphyromonas (Bacteroides) melaninogenicus

Prevotella (Bacteroides) bivius

Susceptibility Testing

For specific information regarding susceptibility test interpretive criteria and associated test methods and quality control standards recognized by FDA for this drug, please see: https://www.fda.gov/STIC.

INDICATIONS AND USAGE

Before instituting treatment with ceftriaxone, appropriate specimens should be obtained for isolation of the causative organism and for determination of its susceptibility to the drug. Therapy may be instituted prior to obtaining results of susceptibility testing.

To reduce the development of drug-resistant bacteria and maintain the effectiveness of ceftriaxone for injection, USP and other antibacterial drugs, ceftriaxone for injection, USP should be used only to treat or prevent infections that are proven or strongly suspected to be caused by susceptible bacteria. When culture and susceptibility information are available, they should be considered in selecting or modifying antibacterial therapy. In the absence of such data, local epidemiology and susceptibility patterns may contribute to the empiric selection of therapy.

Ceftriaxone for injection, USP is indicated for the treatment of the following infections when caused by susceptible organisms:

Lower Respiratory Tract Infections

Caused by Streptococcus pneumoniae, Staphylococcus aureus, Haemophilus influenzae, Haemophilus parainfluenzae, Klebsiella pneumoniae, Escherichia coli, Enterobacter aerogenes, Proteus mirabilisor Serratia marcescens.

Acute Bacterial Otitis Media

Caused by Streptococcus pneumoniae, Haemophilus influenzae(including beta-lactamase producing strains) or Moraxella catarrhalis(including beta-lactamase producing strains).

NOTE: In one study lower clinical cure rates were observed with a single dose of ceftriaxone compared to 10 days of oral therapy. In a second study comparable cure rates were observed between single dose ceftriaxone and the comparator. The potentially lower clinical cure rate of ceftriaxone should be balanced against the potential advantages of parenteral therapy (see CLINICAL STUDIES).

Skin and Skin Structure Infections

Caused by Staphylococcus aureus, Staphylococcus epidermidis, Streptococcus pyogenes, Viridans group streptococci, Escherichia coli, Enterobacter cloacae, Klebsiella oxytoca, Klebsiella pneumoniae, Proteus mirabilis, Morganella morganii*, Pseudomonas aeruginosa, Serratia marcescens, Acinetobacter calcoaceticus, Bacteroides fragilis*or Peptostreptococcusspecies.

Urinary Tract Infections (complicated and uncomplicated)

Caused by Escherichia coli, Proteus mirabilis, Proteus vulgaris, Morganella morganiior Klebsiella pneumoniae.

Uncomplicated Gonorrhea (cervical/urethral and rectal)

Caused by Neisseria gonorrhoeae, including both penicillinase- and nonpenicillinase-producing strains, and pharyngeal gonorrhea caused by nonpenicillinase-producing strains of Neisseria gonorrhoeae.

Pelvic Inflammatory Disease

Caused by Neisseria gonorrhoeae. Ceftriaxone sodium, like other cephalosporins, has no activity against Chlamydia trachomatis. Therefore, when cephalosporins are used in the treatment of patients with pelvic inflammatory disease and Chlamydia trachomatisis one of the suspected pathogens, appropriate antichlamydial coverage should be added.

Bacterial Septicemia

Caused by Staphylococcus aureus, Streptococcus pneumoniae, Escherichia coli, Haemophilus influenzaeor Klebsiella pneumoniae.

Bone and Joint Infections

Caused by Staphylococcus aureus, Streptococcus pneumoniae, Escherichia coli, Proteus mirabilis, Klebsiella pneumoniaeor Enterobacterspecies.

Intra-abdominal Infections

Caused by Escherichia coli, Klebsiella pneumoniae, Bacteroides fragilis, Clostridiumspecies (Note: most strains of Clostridium difficileare resistant) or Peptostreptococcusspecies.

Meningitis

Caused by Haemophilus influenzae, Neisseria meningitidisor Streptococcus pneumoniae. Ceftriaxone has also been used successfully in a limited number of cases of meningitis and shunt infection caused by Staphylococcus epidermidis*and Escherichia coli*.

*Efficacy for this organism in this organ system was studied in fewer than ten infections.

Surgical Prophylaxis

The preoperative administration of a single 1 g dose of ceftriaxone may reduce the incidence of postoperative infections in patients undergoing surgical procedures classified as contaminated or potentially contaminated (e.g., vaginal or abdominal hysterectomy or cholecystectomy for chronic calculous cholecystitis in high-risk patients, such as those over 70 years of age, with acute cholecystitis not requiring therapeutic antimicrobials, obstructive jaundice or common duct bile stones) and in surgical patients for whom infection at the operative site would present serious risk (e.g., during coronary artery bypass surgery). Although ceftriaxone has been shown to have been as effective as cefazolin in the prevention of infection following coronary artery bypass surgery, no placebo-controlled trials have been conducted to evaluate any cephalosporin antibiotic in the prevention of infection following coronary artery bypass surgery.

When administered prior to surgical procedures for which it is indicated, a single 1 g dose of ceftriaxone provides protection from most infections due to susceptible organisms throughout the course of the procedure.

CONTRAINDICATIONS

Hypersensitivity

Ceftriaxone for injection is contraindicated in patients with known hypersensitivity to ceftriaxone, any of its excipients or to any other cephalosporin. Patients with previous hypersensitivity reactions to penicillin and other beta lactam antibacterial agents may be at greater risk of hypersensitivity to ceftriaxone (see Warnings – Hypersensitivity Reactions).

Neonates

Premature neonates: Ceftriaxone for injection is contraindicated in premature neonates up to a post-menstrual age of 41 weeks (gestational age + chronological age).

Hyperbilirubinemic neonates: Hyperbilirubinemic neonates should not be treated with ceftriaxone for injection. Ceftriaxone can displace bilirubin from its binding to serum albumin, leading to a risk of bilirubin encephalopathy in these patients.

Neonates Requiring Calcium Containing IV Solutions

Ceftriaxone for injection is contraindicated in neonates (≤ 28 days) if they require (or are expected to require) treatment with calcium-containing IV solutions, including continuous calcium-containing infusions such as parenteral nutrition because of the risk of precipitation of ceftriaxone-calcium (see CLINICAL PHARMACOLOGY, WARNINGSand DOSAGE AND ADMINISTRATION).

Cases of fatal outcomes in which a crystalline material was observed in the lungs and kidneys at autopsy have been reported in neonates receiving ceftriaxone for injection and calcium-containing fluids.

In some of these cases, the same intravenous infusion line was used for both ceftriaxone for injection and calcium-containing fluids and in some a precipitate was observed in the intravenous infusion line. There have been no similar reports in patients other than neonates.

Lidocaine

Intravenous administration of ceftriaxone solutions containing lidocaine is contraindicated. When lidocaine solution is used as a solvent with ceftriaxone for intramuscular injection, exclude all contraindications to lidocaine. Refer to the prescribing information of lidocaine.

WARNINGS

Hypersensitivity Reactions

Before therapy with ceftriaxone for injection is instituted, careful inquiry should be made to determine whether the patient has had previous hypersensitivity reactions to cephalosporins, penicillins and other beta-lactam agents or other drugs. This product should be given cautiously to penicillin and other beta-lactam agent-sensitive patients. Antibacterial drugs should be administered with caution to any patient who has demonstrated some form of allergy, particularly to drugs. Serious acute hypersensitivity reactions may require the use of subcutaneous epinephrine and other emergency measures.

As with all beta-lactam antibacterial agents, serious and occasionally fatal hypersensitivity reactions (i.e., anaphylaxis) have been reported. In case of severe hypersensitivity reactions, treatment with ceftriaxone must be discontinued immediately and adequate emergency measures must be initiated.

Interaction with Calcium-Containing Products

Do not use diluents containing calcium, such as Ringer’s solution or Hartmann’s solution, to reconstitute ceftriaxone vials or to further dilute a reconstituted vial for IV administration because a precipitate can form. Precipitation of ceftriaxone-calcium can also occur when ceftriaxone is mixed with calcium-containing solutions in the same IV administration line. Ceftriaxone must not be administered simultaneously with calcium-containing IV solutions, including continuous calcium-containing infusions such as parenteral nutrition via a Y-site. However, in patients other than neonates, ceftriaxone and calcium-containing solutions may be administered sequentially of one another if the infusion lines are thoroughly flushed between infusions with a compatible fluid. In vitrostudies using adult and neonatal plasma from umbilical cord blood demonstrated that neonates have an increased risk of precipitation of ceftriaxone-calcium (see CLINICAL PHARMACOLOGY, CONTRAINDICATIONSand DOSAGE AND ADMINISTRATION).

Neurological Adverse Reactions

Serious neurological adverse reactions have been reported during postmarketing surveillance with ceftriaxone use. These reactions include encephalopathy (disturbance of consciousness including somnolence, lethargy, and confusion), seizures, myoclonus, and non-convulsive status epilepticus (see ADVERSE REACTIONS). Some cases occurred in patients with severe renal impairment who did not receive appropriate dosage adjustment. However, in other cases, neurological adverse reactions occurred in patients receiving an appropriate dosage adjustment. The neurological adverse reactions were reversible and resolved after discontinuation. If neurological adverse reactions associated with ceftriaxone for injection therapy occur, discontinue ceftriaxone for injection and institute appropriate supportive measures. Make appropriate dosage adjustments in patients with severe renal impairment (see DOSAGE AND ADMINISTRATION).

Clostridium difficile-Associated Diarrhea

Clostridium difficileassociated diarrhea (CDAD) has been reported with use of nearly all antibacterial agents, including ceftriaxone, and may range in severity from mild diarrhea to fatal colitis. Treatment with antibacterial agents alters the normal flora of the colon leading to overgrowth of C. difficile.

C. difficileproduces toxins A and B which contribute to the development of CDAD. Hypertoxin producing strains of C. difficilecause increased morbidity and mortality, as these infections can be refractory to antimicrobial therapy and may require colectomy. CDAD must be considered in all patients who present with diarrhea following antibiotic use. Careful medical history is necessary since CDAD has been reported to occur over two months after the administration of antibacterial agents.

If CDAD is suspected or confirmed, ongoing antibiotic use not directed against C. difficilemay need to be discontinued. Appropriate fluid and electrolyte management, protein supplementation, antibiotic treatment of C. difficile, and surgical evaluation should be instituted as clinically indicated.

Hemolytic Anemia

An immune mediated hemolytic anemia has been observed in patients receiving cephalosporin class antibacterials including ceftriaxone. Severe cases of hemolytic anemia, including fatalities, have been reported during treatment in both adults and children. If a patient develops anemia while on ceftriaxone, the diagnosis of a cephalosporin associated anemia should be considered and ceftriaxone stopped until the etiology is determined.

PRECAUTIONS

Information for Patients

- Advise patients that neurological adverse reactions could occur with ceftriaxone for injection use. Instruct patients or their caregivers to inform their healthcare provider at once of any neurological signs and symptoms, including encephalopathy (disturbance of consciousness including somnolence, lethargy, and confusion), seizures, myoclonus, and nonconvulsive status epilepticus, for immediate treatment, or discontinuation of ceftriaxone for injection (see WARNINGSand PRECAUTIONS).

Development of Drug-resistant Bacteria

Prescribing ceftriaxone in the absence of a proven or strongly suspected bacterial infection or a prophylactic indication is unlikely to provide benefit to the patient and increases the risk of the development of drug-resistant bacteria. Prolonged use of ceftriaxone may result in overgrowth of non-susceptible organisms. Careful observation of the patient is essential. If superinfection occurs during therapy, appropriate measures should be taken.

Patients with Renal or Hepatic Impairment

Ceftriaxone is excreted via both biliary and renal excretion (see CLINICAL PHARMACOLOGY). Therefore, patients with renal failure normally require no adjustment in dosage when usual doses of ceftriaxone are administered.

Dosage adjustments should not be necessary in patients with hepatic dysfunction; however, in patients with both hepatic dysfunction and significant renal disease, caution should be exercised and the ceftriaxone dosage should not exceed 2 g daily.

Ceftriaxone is not removed by peritoneal- or hemodialysis. In patients undergoing dialysis no additional supplementary dosing is required following the dialysis. In patients with both severe renal and hepatic dysfunction, close clinical monitoring for safety and efficacy is advised.

Effect on Prothrombin Time

Alterations in prothrombin times have occurred in patients treated with ceftriaxone. Monitor prothrombin time during ceftriaxone treatment in patients with impaired vitamin K synthesis or low vitamin K stores (e.g., chronic hepatic disease and malnutrition). Vitamin K administration (10 mg weekly) may be necessary if the prothrombin time is prolonged before or during therapy.

Concomitant use of ceftriaxone with Vitamin K antagonists may increase the risk of bleeding. Coagulation parameters should be monitored frequently, and the dose of the anticoagulant adjusted accordingly, both during and after treatment with ceftriaxone (see ADVERSE REACTIONS).

Gallbladder Pseudolithiasis

Ceftriaxone-calcium precipitates in the gallbladder have been observed in patients receiving ceftriaxone. These precipitates appear on sonography as an echo without acoustical shadowing suggesting sludge or as an echo with acoustical shadowing which may be misinterpreted as gallstones. The probability of such precipitates appears to be greatest in pediatric patients. Patients may be asymptomatic or may develop symptoms of gallbladder disease. The condition appears to be reversible upon discontinuation of ceftriaxone sodium and institution of conservative management. Discontinue ceftriaxone sodium in patients who develop signs and symptoms suggestive of gallbladder disease and/or the sonographic findings described above.

Urolithiasis and Post-Renal Acute Renal Failure

Ceftriaxone-calcium precipitates in the urinary tract have been observed in patients receiving ceftriaxone and may be detected as sonographic abnormalities. The probability of such precipitates appears to be greatest in pediatric patients. Patients may be asymptomatic or may develop symptoms of urolithiasis, and ureteral obstruction and post-renal acute renal failure. The condition appears to be reversible upon discontinuation of ceftriaxone sodium and institution of appropriate management. Ensure adequate hydration in patients receiving ceftriaxone. Discontinue ceftriaxone in patients who develop signs and symptoms suggestive of urolithiasis, oliguria or renal failure and/or the sonographic findings described above.

Pancreatitis

Cases of pancreatitis, possibly secondary to biliary obstruction, have been reported in patients treated with ceftriaxone. Most patients presented with risk factors for biliary stasis and biliary sludge (preceding major therapy, severe illness, total parenteral nutrition). A cofactor role of ceftriaxone-related biliary precipitation cannot be ruled out.

Information for Patients

- Patients should be counseled that antibacterial drugs including ceftriaxone for injection should only be used to treat bacterial infections. They do not treat viral infections (e.g., common cold).
- When ceftriaxone for injection is prescribed to treat a bacterial infection, patients should be told that although it is common to feel better early in the course of therapy, the medication should be taken exactly as directed. Skipping doses or not completing the full course of therapy may (1) decrease the effectiveness of the immediate treatment and (2) increase the likelihood that bacteria will develop resistance and will not be treatable by ceftriaxone for injection or other antibacterial drugs in the future.
- Diarrhea is a common problem caused by antibiotics which usually ends when the antibiotic is discontinued. Sometimes after starting treatment with antibiotics, patients can develop watery and bloody stools (with or without stomach cramps and fever) even as late as two or more months after having taken the last dose of the antibiotic. If this occurs, patients should contact their physician as soon as possible.

Repackaged By / Distributed By: RemedyRepack Inc.

625 Kolter Drive, Indiana, PA 15701

(724) 465-8762

Carcinogenesis, Mutagenesis, Impairment of Fertility

Carcinogenesis

Considering the maximum duration of treatment and the class of the compound, carcinogenicity studies with ceftriaxone in animals have not been performed. The maximum duration of animal toxicity studies was 6 months.

Mutagenesis

Genetic toxicology tests included the Ames test, a micronucleus test and a test for chromosomal aberrations in human lymphocytes cultured in vitrowith ceftriaxone. Ceftriaxone showed no potential for mutagenic activity in these studies.

Impairment of Fertility

Ceftriaxone produced no impairment of fertility when given intravenously to rats at daily doses up to 586 mg/kg/day, approximately 20 times the recommended clinical dose of 2 g/day.

Pregnancy

Teratogenic Effects

Reproductive studies have been performed in mice and rats at doses up to 20 times the usual human dose and have no evidence of embryotoxicity, fetotoxicity or teratogenicity. In primates, no embryotoxicity or teratogenicity was demonstrated at a dose approximately 3 times the human dose.

There are, however, no adequate and well-controlled studies in pregnant women. Because animal reproductive studies are not always predictive of human response, this drug should be used during pregnancy only if clearly needed.

Nonteratogenic Effects

In rats, in the Segment I (fertility and general reproduction) and Segment III (perinatal and postnatal) studies with intravenously administered ceftriaxone, no adverse effects were noted on various reproductive parameters during gestation and lactation, including postnatal growth, functional behavior and reproductive ability of the offspring, at doses of 586 mg/kg/day or less.

Nursing Mothers

Low concentrations of ceftriaxone are excreted in human milk. Caution should be exercised when ceftriaxone is administered to a nursing woman.

Pediatric Use

Safety and effectiveness of ceftriaxone in neonates, infants and pediatric patients have been established for the dosages described in the DOSAGE AND ADMINISTRATIONsection. In vitrostudies have shown that ceftriaxone, like some other cephalosporins, can displace bilirubin from serum albumin. Ceftriaxone should not be administered to hyperbilirubinemic neonates, especially prematures (see CONTRAINDICATIONS).

Geriatric Use

Of the total number of subjects in clinical studies of ceftriaxone, 32% were 60 and over. No overall differences in safety or effectiveness were observed between these subjects and younger subjects, and other reported clinical experience has not identified differences in responses between the elderly and younger patients, but greater sensitivity of some older individuals cannot be ruled out.

The pharmacokinetics of ceftriaxone were only minimally altered in geriatric patients compared to healthy adult subjects and dosage adjustments are not necessary for geriatric patients with ceftriaxone dosages up to 2 grams per day provided there is no severe renal and hepatic impairment (see CLINICAL PHARMACOLOGY).

Influence on Diagnostic Tests

In patients treated with ceftriaxone the Coombs’ test may become positive. Ceftriaxone for injection, like other antibacterial drugs, may result in positive test results for galactosemia.

Nonenzymatic methods for the glucose determination in urine may give false-positive results. For this reason, urine-glucose determination during therapy with ceftriaxone should be done enzymatically.

The presence of ceftriaxone may falsely lower estimated blood glucose values obtained with some blood glucose monitoring systems. Please refer to instructions for use for each system. Alternative testing methods should be used if necessary.

ADVERSE REACTIONS

Ceftriaxone is generally well tolerated. In clinical trials, the following adverse reactions, which were considered to be related to ceftriaxone therapy or of uncertain etiology, were observed:

Local Reactions

Pain, induration and tenderness was 1% overall. Phlebitis was reported in <1% after IV administration. The incidence of warmth, tightness or induration was 17% (3/17) after IM administration of 350 mg/mL and 5% (1/20) after IM administration of 250 mg/mL.

General Disorders and Administration Site Conditions

Injection site pain (0.6%)

Hypersensitivity

Rash (1.7%). Less frequently reported (<1%) were pruritus, fever or chills.

Infections and Infestations

Genital fungal infection (0.1%)

Hematologic

Eosinophilia (6%), thrombocytosis (5.1%) and leukopenia (2.1%). Less frequently reported (<1%) were anemia, hemolytic anemia, neutropenia, lymphopenia, thrombocytopenia and prolongation of the prothrombin time.

Blood and Lymphatic Disorders

Granulocytopenia (0.9%), coagulopathy (0.4%)

Gastrointestinal

Diarrhea/loose stools (2.7%). Less frequently reported (<1%) were nausea or vomiting, and dysgeusia. The onset of pseudomembranous colitis symptoms may occur during or after antibacterial treatment (see WARNINGS).

Hepatic

Elevations of aspartate aminotransferase (AST) (3.1%) or alanine aminotransferase (ALT) (3.3%). Less frequently reported (<1%) were elevations of alkaline phosphatase and bilirubin.

Renal

Elevations of the BUN (1.2%). Less frequently reported (<1%) were elevations of creatinine and the presence of casts in the urine.

Central Nervous System

Headache or dizziness were reported occasionally (<1%).

Genitourinary

Moniliasis or vaginitis were reported occasionally (<1%).

Miscellaneous

Diaphoresis and flushing were reported occasionally (<1%).

Investigations

Blood creatinine increased (0.6%).

Other rarely observed adverse reactions (<0.1%) include abdominal pain, agranulocytosis, allergic pneumonitis, anaphylaxis, basophilia, biliary lithiasis, bronchospasm, colitis, dyspepsia, epistaxis, flatulence, gallbladder sludge, glycosuria, hematuria, jaundice, leukocytosis, lymphocytosis, monocytosis, nephrolithiasis, palpitations, a decrease in the prothrombin time, renal precipitations, seizures, and serum sickness.

Post-Marketing Experience

In addition to the adverse reactions reported during clinical trials, the following adverse experiences have been reported during clinical practice in patients treated with ceftriaxone. Data are generally insufficient to allow an estimate of incidence or to establish causation.

A small number of cases of fatal outcomes in which a crystalline material was observed in the lungs and kidneys at autopsy have been reported in neonates receiving ceftriaxone and calcium-containing fluids. In some of these cases, the same intravenous infusion line was used for both ceftriaxone and calcium-containing fluids and in some a precipitate was observed in the intravenous infusion line. At least one fatality has been reported in a neonate in whom ceftriaxone and calcium-containing fluids were administered at different time points via different intravenous lines; no crystalline material was observed at autopsy in this neonate. There have been no similar reports in patients other than neonates.

Gastrointestinal

Pancreatitis, stomatitis and glossitis.

Genitourinary

Oliguria, ureteric obstruction, post-renal acute renal failure.

Dermatologic

Exanthema, allergic dermatitis, urticaria, edema; acute generalized exanthematous pustulosis (AGEP) and isolated cases of severe cutaneous adverse reactions (erythema multiforme, Stevens-Johnson syndrome or Lyell’s syndrome/toxic epidermal necrolysis) have been reported.

Hematological Changes

Isolated cases of agranulocytosis (< 500/mm^3) have been reported, most of them after 10 days of treatment and following total doses of 20 g or more.

Neurologic

Encephalopathy, seizures, myoclonus, and non-convulsive status epilepticus (see WARNINGSand PRECAUTIONS).

Other, Adverse Reactions

Symptomatic precipitation of ceftriaxone calcium salt in the gallbladder, kernicterus, oliguria, and anaphylactic or anaphylactoid reactions.

Cephalosporin Class Adverse Reactions

In addition to the adverse reactions listed above which have been observed in patients treated with ceftriaxone, the following adverse reactions and altered laboratory test results have been reported for cephalosporin class antibiotics:

Adverse Reactions

Allergic reactions, drug fever, serum sickness-like reaction, renal dysfunction, toxic nephropathy, reversible hyperactivity, hypertonia, hepatic dysfunction including cholestasis, aplastic anemia, hemorrhage, and superinfection.

Altered Laboratory Tests

Positive direct Coombs’ test, false-positive test for urinary glucose, and elevated LDH (see PRECAUTIONS).

Several cephalosporins have been implicated in triggering seizures, particularly in patients with renal impairment when the dosage was not reduced (see DOSAGE AND ADMINISTRATION). If seizures associated with drug therapy occur, the drug should be discontinued. Anticonvulsant therapy can be given if clinically indicated.

OVERDOSAGE

Ceftriaxone overdosage has been reported in patients with severe renal impairment. Reactions have included neurological outcomes, including encephalopathy, seizures, myoclonus, and non-convulsive status epilepticus. In the event of overdosage, discontinue ceftriaxone for injection therapy and provide general supportive treatment (see DOSAGE AND ADMINISTRATION, WARNINGSand PRECAUTIONS).

In the case of overdosage, drug concentration would not be reduced by hemodialysis or peritoneal dialysis. There is no specific antidote. Treatment of overdosage should be symptomatic.

DOSAGE AND ADMINISTRATION

Ceftriaxone may be administered intravenously or intramuscularly.

Do not use diluents containing calcium, such as Ringer’s solution or Hartmann’s solution, to reconstitute ceftriaxone vials or to further dilute a reconstituted vial for IV administration because a precipitate can form. Precipitation of ceftriaxone-calcium can also occur when ceftriaxone is mixed with calcium-containing solutions in the same IV administration line.

Ceftriaxone must not be administered simultaneously with calcium-containing IV solutions, including continuous calcium-containing infusions such as parenteral nutrition via a Y-site. However, in patients other than neonates, ceftriaxone and calcium-containing solutions may be administered sequentially of one another if the infusion lines are thoroughly flushed between infusions with a compatible fluid (see WARNINGS).

There have been no reports of an interaction between ceftriaxone and oral calcium-containing products or interaction between intramuscular ceftriaxone and calcium-containing products (IV or oral).

Neonates

Hyperbilirubinemic neonates, especially prematures, should not be treated with ceftriaxone for injection. Ceftriaxone is contraindicated in premature neonates (see CONTRAINDICATIONS).

Ceftriaxone is contraindicated in neonates (≤ 28 days) if they require (or are expected to require) treatment with calcium-containing IV solutions, including continuous calcium-containing infusions such as parenteral nutrition because of the risk of precipitation of ceftriaxone-calcium (see CONTRAINDICATIONS).

Intravenous doses should be given over 60 minutes in neonates to reduce the risk of bilirubin encephalopathy.

Pediatric Patients

For the treatment of skin and skin structure infections, the recommended total daily dose is 50 to 75 mg/kg given once a day (or in equally divided doses twice a day). The total daily dose should not exceed 2 grams.

For the treatment of acute bacterial otitis media, a single intramuscular dose of 50 mg/kg (not to exceed 1 gram) is recommended (see INDICATIONS AND USAGE).

For the treatment of serious miscellaneous infections other than meningitis, the recommended total daily dose is 50 to 75 mg/kg, given in divided doses every 12 hours. The total daily dose should not exceed 2 grams.

In the treatment of meningitis, it is recommended that the initial therapeutic dose be 100 mg/kg (not to exceed 4 grams). Thereafter, a total daily dose of 100 mg/kg/day (not to exceed 4 grams daily) is recommended. The daily dose may be administered once a day (or in equally divided doses every 12 hours). The usual duration of therapy is 7 to 14 days.

Adults

The usual adult daily dose is 1 to 2 grams given once a day (or in equally divided doses twice a day) depending on the type and severity of infection. The total daily dose should not exceed 4 grams.

If Chlamydia trachomatisis a suspected pathogen, appropriate antichlamydial coverage should be added, because ceftriaxone sodium has no activity against this organism.

For the treatment of uncomplicated gonococcal infections, a single intramuscular dose of 250 mg is recommended.

For preoperative use (surgical prophylaxis), a single dose of 1 gram administered intravenously 1/2 to 2 hours before surgery is recommended.

Generally, ceftriaxone therapy should be continued for at least 2 days after the signs and symptoms of infection have disappeared. The usual duration of therapy is 4 to 14 days; in complicated infections, longer therapy may be required.

When treating infections caused by Streptococcus pyogenes, therapy should be continued for at least 10 days.

No dosage adjustment is necessary for patients with impairment of renal or hepatic function (see PRECAUTIONS).

The dosages recommended for adults require no modification in elderly patients, up to 2 g per day, provided there is no severe renal and hepatic impairment (see PRECAUTIONS).

Directions for Use

Intramuscular Administration

Reconstitute ceftriaxone sodium powder with the appropriate diluent (see DOSAGE AND ADMINISTRATION: Compatibility and Stability).

Inject diluent into vial, shake vial thoroughly to form solution. Withdraw entire contents of vial into syringe to equal total labeled dose.

After reconstitution, each 1 mL of solution contains approximately 250 mg or 350 mg equivalent of ceftriaxone according to the amount of diluent indicated below. If required, more dilute solutions could be utilized. A 350 mg/mL concentration is not recommended for the 250 mg vial since it may not be possible to withdraw the entire contents.

As with all intramuscular preparations, ceftriaxone should be injected well within the body of a relatively large muscle; aspiration helps to avoid unintentional injection into a blood vessel.

Vial Dosage Size | Amount of Diluent to be Added
Vial Dosage Size | 250 mg/mL | 350 mg/mL
250 mg | 0.9 mL | –
500 mg | 1.8 mL | 1 mL
1 g | 3.6 mL | 2.1 mL
2 g | 7.2 mL | 4.2 mL

Intravenous Administration

Ceftriaxone should be administered intravenously by infusion over a period of 30 minutes, except in neonates where administration over 60 minutes is recommended to reduce the risk of bilirubin encephalopathy. Concentrations between 10 mg/mL and 40 mg/mL are recommended; however, lower concentrations may be used if desired. Reconstitute vials with an appropriate IV diluent (see DOSAGE AND ADMINISTRATION: Compatibility and Stability).

Vial Dosage Size | Amount of Diluent to be Added
250 mg | 2.4 mL
500 mg | 4.8 mL
1 g | 9.6 mL
2 g | 19.2 mL

After reconstitution, each 1 mL of solution contains approximately 100 mg equivalent of ceftriaxone. Withdraw entire contents and dilute to the desired concentration with the appropriate IV diluent.

Compatibility and Stability

Do not use diluents containing calcium, such as Ringer’s solution or Hartmann’s solution, to reconstitute ceftriaxone for injection vials or to further dilute a reconstituted vial for IV administration. Particulate formation can result.

Ceftriaxone has been shown to be compatible with Flagyl® IV (metronidazole hydrochloride). The concentration should not exceed 5 to 7.5 mg/mL metronidazole hydrochloride with ceftriaxone 10 mg/mL as an admixture. The admixture is stable for 24 hours at room temperature only in 0.9% sodium chloride injection or 5% dextrose in water (D5W). No compatibility studies have been conducted with the Flagyl® IV RTU® (metronidazole) formulation or using other diluents. Metronidazole at concentrations greater than 8 mg/mL will precipitate. Do not refrigerate the admixture as precipitation will occur.

Vancomycin, amsacrine, aminoglycosides, and fluconazole are incompatible with ceftriaxone in admixtures. When any of these drugs are to be administered concomitantly with ceftriaxone by intermittent intravenous infusion, it is recommended that they be given sequentially, with thorough flushing of the intravenous lines (with one of the compatible fluids) between the administrations.

Ceftriaxone for injection solutions should notbe physically mixed with or piggybacked into solutions containing other antimicrobial drugs or into diluent solutions other than those listed above, due to possible incompatibility (see WARNINGS).

Ceftriaxone sodium sterile powder should be stored at 20° to 25°C (68° to 77°F) [see USP Controlled Room Temperature] and protected from light. After reconstitution, protection from normal light is not necessary. The color of solutions ranges from light yellow to amber, depending on the length of storage, concentration and diluent used.

Ceftriaxone intramuscularsolutions remain stable (loss of potency less than 10%) for the following time periods:

Diluent | Concentration | Storage
Diluent | mg/mL | Room Temperature; (25°C) | Refrigerated; (4°C)
Sterile Water for Injection | 100; 250, 350 | 2 days; 24 hours | 10 days; 3 days
0.9% Sodium Chloride Solution | 100; 250, 350 | 2 days; 24 hours | 10 days; 3 days
5% Dextrose Solution | 100; 250, 350 | 2 days; 24 hours | 10 days; 3 days
Bacteriostatic Water + 0.9% Benzyl Alcohol | 100; 250, 350 | 24 hours; 24 hours | 10 days; 3 days
1% Lidocaine Solution (without epinephrine) | 100; 250, 350 | 24 hours; 24 hours | 10 days; 3 days

Ceftriaxone intravenoussolutions, at concentrations of 10, 20 and 40 mg/mL, remain stable (loss of potency less than 10%) for the following time periods stored in glass or PVC containers:

Diluent | Storage
Diluent | Room Temperature; (25°C) | Refrigerated; (4°C)
Sterile Water | 2 days | 10 days
0.9% Sodium; Chloride Solution | 2 days | 10 days
5% Dextrose Solution | 2 days | 10 days
10% Dextrose Solution | 2 days | 10 days
5% Dextrose + 0.9%; Sodium Chloride Solution | 2 days | Incompatible
5% Dextrose + 0.45%; Sodium Chloride Solution | 2 days | Incompatible

* Data available for 10 to 40 mg/mL concentrations in this diluent in PVC containers only.

The following intravenousceftriaxone solutions are stable at room temperature (25°C) for 24 hours, at concentrations between 10 mg/mL and 40 mg/mL: Sodium Lactate (PVC container), 10% Invert Sugar (glass container), 5% Sodium Bicarbonate (glass container), Freamine III (glass container), Normosol-M in 5% Dextrose (glass and PVC containers), Ionosol-B in 5% Dextrose (glass container), 5% Mannitol (glass container), 10% Mannitol (glass container).

After the indicated stability time periods, unused portions of solutions should be discarded.

NOTE: Parenteral drug products should be inspected visually for particulate matter before administration.

Ceftriaxone reconstituted with 5% Dextrose or 0.9% Sodium Chloride solution at concentrations between 10 mg/mL and 40 mg/mL, and then stored in frozen state (-20°C) in PVC or polyolefin containers, remains stable for 26 weeks.

Frozen solutions of ceftriaxone for injection should be thawed at room temperature before use. After thawing, unused portions should be discarded. DO NOT REFREEZE.

ANIMAL PHARMACOLOGY

Concretions consisting of the precipitated calcium salt of ceftriaxone have been found in the gallbladder bile of dogs and baboons treated with ceftriaxone.

These appeared as a gritty sediment in dogs that received 100 mg/kg/day for 4 weeks. A similar phenomenon has been observed in baboons but only after a protracted dosing period (6 months) at higher dose levels (335 mg/kg/day or more). The likelihood of this occurrence in humans is considered to be low, since ceftriaxone has a greater plasma half-life in humans, the calcium salt of ceftriaxone is more soluble in human gallbladder bile and the calcium content of human gallbladder bile is relatively low.

HOW SUPPLIED

Ceftriaxone for injection, USP is supplied as a sterile crystalline powder in glass vials as follows:

Vials containing 1 g equivalent to ceftriaxone. Package of 10

NDC: 70518-2499-00

NDC: 70518-2499-01

PACKAGING: 10 in 1 CARTON

PACKAGING: 1 in 1 VIAL SINGLE USE, TYPE 0

Storage Prior to Reconstitution

Store at 20° to 25°C (68° to 77°F) [see USP Controlled Room Temperature]. Protect from light.

Repackaged and Distributed By:

Remedy Repack, Inc.

625 Kolter Dr. Suite #4 Indiana, PA 1-724-465-8762

CLINICAL STUDIES

Clinical Trials in Pediatric Patients with Acute Bacterial Otitis Media

In two adequate and well-controlled US clinical trials a single IM dose of ceftriaxone was compared with a 10 day course of oral antibiotic in pediatric patients between the ages of 3 months and 6 years. The clinical cure rates and statistical outcome appear in the table below:

Table 5. Clinical Efficacy in Pediatric Patients with Acute Bacterial Otitis Media
Clinical Efficacy in Evaluable Population
Study Day | Ceftriaxone; Single-Dose | Comparator-; 10 Days of; Oral Therapy | 95%; Confidence; Interval | Statistical; Outcome
Study 1 – US |  | amoxicillin/; clavulanate |  | Ceftriaxone is lower than control at study day 14 and 28.
14 | 74% (220/296) | 82% (247/302) | (-14.4%, -0.5%) | Ceftriaxone is lower than control at study day 14 and 28.
28 | 58% (167/288) | 67% (200/297) | (-17.5%, -1.2%) | Ceftriaxone is lower than control at study day 14 and 28.
Study 2 – US^1 |  | TMP-SMZ |  | Ceftriaxone is equivalent to control at study day 14 and 28.
14 | 54% (113/210) | 60% (124/206) | (-16.4%, 3.6%) | Ceftriaxone is equivalent to control at study day 14 and 28.
28 | 35% (73/206) | 45% (93/205) | (-19.9%, 0.0%) | Ceftriaxone is equivalent to control at study day 14 and 28.

An open-label bacteriologic study of ceftriaxone without a comparator enrolled 108 pediatric patients, 79 of whom had positive baseline cultures for one or more of the common pathogens. The results of this study are tabulated as follows:

Week 2 and 4 Bacteriologic Eradication Rates in the Per Protocol Analysis in the Roche Bacteriologic Study by pathogen:

Table 6. Bacteriologic Eradication Rates by Pathogen
Organism | Study Day; 13 to 15 |  | Study Day; 30+2
Organism | No.; Analyzed | No. Erad.; (%) | No.; Analyzed | No. Erad.; (%)
Streptococcus pneumoniae | 38 | 32 (84) | 35 | 25 (71)
Haemophilus influenzae | 33 | 28 (85) | 31 | 22 (71)
Moraxella catarrhalis | 15 | 12 (80) | 15 | 9 (60)

REFERENCES

Flagyl®is a registered trademark of G.D. Searle & Co.

Repackaged and Distributed By:

Remedy Repack, Inc.

625 Kolter Dr. Suite #4 Indiana, PA 1-724-465-8762

PACKAGE LABEL

DRUG: Ceftriaxone Sodium

GENERIC: Ceftriaxone Sodium

DOSAGE: INJECTION, POWDER, FOR SOLUTION

ADMINSTRATION: INTRAVENOUS

NDC: 70518-2499-0

PACKAGING: 1 in 1 VIAL, SINGLE-USE

OUTER PACKAGING: 10 in 1 CARTON

ACTIVE INGREDIENT(S):

- CEFTRIAXONE SODIUM 1g in 1

INACTIVE INGREDIENT(S):